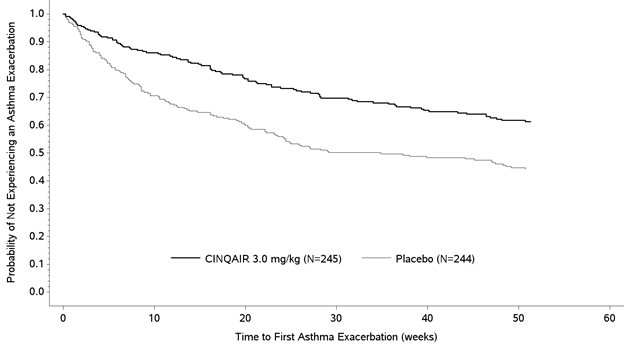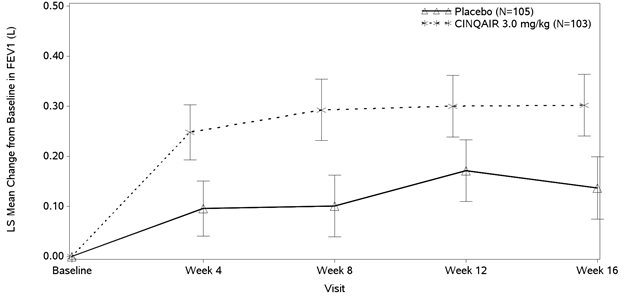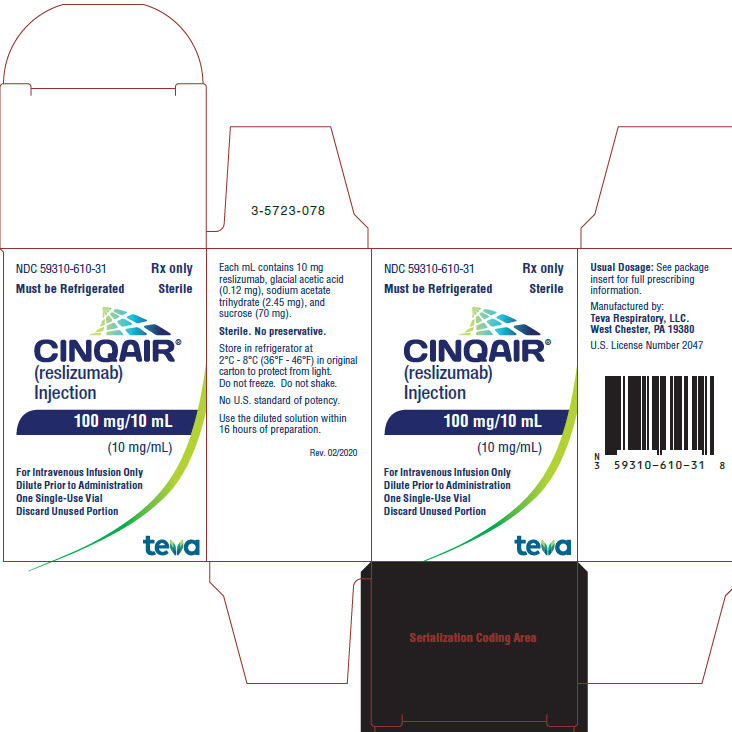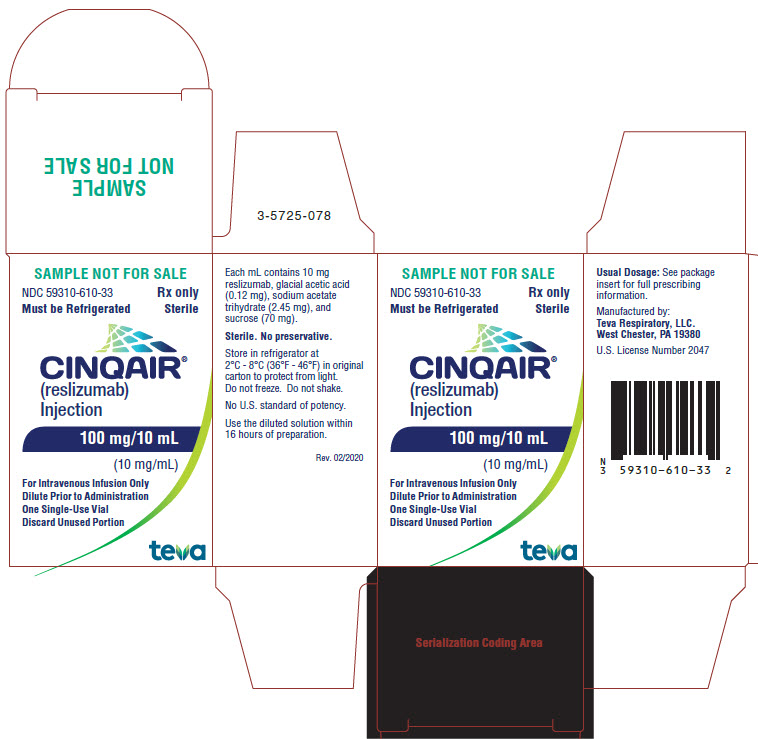 DRUG LABEL: CINQAIR
NDC: 59310-610 | Form: INJECTION, SOLUTION, CONCENTRATE
Manufacturer: Teva Respiratory, LLC
Category: prescription | Type: HUMAN PRESCRIPTION DRUG LABEL
Date: 20251117

ACTIVE INGREDIENTS: RESLIZUMAB 10 mg/1 mL
INACTIVE INGREDIENTS: ACETIC ACID; SODIUM ACETATE; SUCROSE; WATER

HIGHLIGHTS OF PRESCRIBING INFORMATION

These highlights do not include all the information needed to use CINQAIR safely and effectively. See full prescribing information for CINQAIR.
CINQAIR® (reslizumab) injection, for intravenous use
Initial U.S. Approval: 2016

WARNING: ANAPHYLAXIS

See full prescribing information for complete boxed warning.

- Anaphylaxis occurred with CINQAIR infusion in 0.3% of patients in placebo-controlled studies (5.1)
- Patients should be observed for an appropriate period of time after CINQAIR infusion; healthcare professionals should be prepared to manage anaphylaxis that can be life-threatening (5.1)
- Discontinue CINQAIR immediately if the patient experiences anaphylaxis (5.1)

1 INDICATIONS AND USAGE

CINQAIR is an interleukin-5 antagonist monoclonal antibody (IgG4 kappa) indicated for add-on maintenance treatment of patients with severe asthma aged 18 years and older, and with an eosinophilic phenotype (1).

Limitations of Use: CINQAIR is not indicated for:

- treatment of other eosinophilic conditions (1)
- relief of acute bronchospasm or status asthmaticus (1)

2 DOSAGE AND ADMINISTRATION

- CINQAIR is for intravenous infusion only. Do not administer as an intravenous push or bolus (2.1)
- CINQAIR should be administered by a healthcare professional prepared to manage anaphylaxis (2.2)
- Recommended dosage regimen is 3 mg/kg once every 4 weeks by intravenous infusion over 20-50 minutes (2.1)

3 DOSAGE FORMS AND STRENGTHS

Injection: 100 mg/10 mL (10 mg/mL) solution in single-use vials (3)

4 CONTRAINDICATIONS

Known hypersensitivity to reslizumab or any of its excipients (4)

5 WARNINGS AND PRECAUTIONS

- Malignancy: Malignancies were observed in clinical studies. (5.3)
- Reduction in Corticosteroid Dosage: Do not discontinue systemic or inhaled corticosteroids abruptly upon initiation of therapy with CINQAIR. Decrease corticosteroids gradually, if appropriate. (5.4)
- Parasitic (Helminth) Infection: Treat patients with pre-existing helminth infections before therapy with CINQAIR. If patients become infected while receiving CINQAIR and do not respond to anti-helminth treatment, discontinue CINQAIR until the parasitic infection resolves. (5.5)

6 ADVERSE REACTIONS

The most common adverse reaction (incidence greater than or equal to 2%) includes oropharyngeal pain. (6.1).

To report SUSPECTED ADVERSE REACTIONS, contact Teva Pharmaceuticals at 1-888-483-8279 or FDA at 1-800-FDA-1088 or www.fda.gov/medwatch.

FULL PRESCRIBING INFORMATION

WARNING: ANAPHYLAXIS

Anaphylaxis has been observed with CINQAIR infusion in 0.3% of patients in placebo-controlled clinical studies. Anaphylaxis was reported as early as the second dose of CINQAIR [see Warnings and Precautions (5.1), Adverse Reactions (6)].

Anaphylaxis can be life-threatening. Patients should be observed for an appropriate period of time after CINQAIR administration by a healthcare professional prepared to manage anaphylaxis. Discontinue CINQAIR immediately if the patient experiences signs or symptoms of anaphylaxis [see Dosage and Administration (2.2), Warnings and Precautions (5.1)].

1 INDICATIONS AND USAGE

CINQAIR® is indicated for the add-on maintenance treatment of patients with severe asthma aged 18 years and older with an eosinophilic phenotype [see Clinical Studies (14)].

Limitation of Use:

- CINQAIR is not indicated for treatment of other eosinophilic conditions.
- CINQAIR is not indicated for the relief of acute bronchospasm or status asthmaticus [see Warnings and Precautions (5.2)].

2 DOSAGE AND ADMINISTRATION

2.1 Dosing

CINQAIR is for intravenous infusion only. Do not administer as an intravenous push or bolus.

The recommended dosage regimen is 3 mg/kg once every 4 weeks administered by intravenous infusion over 20-50 minutes [see Dosage and Administration (2.2)].

Discontinue the infusion immediately if the patient experiences a severe systemic reaction, including anaphylaxis [see Contraindications (4), Warnings and Precautions (5.1)].

2.2 Preparation and Administration Instructions

CINQAIR is provided as a solution in a single-use vial for intravenous infusion only and should be prepared by a healthcare professional using aseptic technique as follows:

Preparation of intravenous infusion

1. Remove CINQAIR from the refrigerator. To minimize foaming, do not shake CINQAIR.
2. Inspect visually for particulate matter and discoloration prior to administration. CINQAIR solution is clear to slightly hazy/opalescent, colorless to slightly yellow liquid. Since CINQAIR is a protein, proteinaceous particles may be present in the solution that appear as translucent to white, amorphous particulates. Do not administer if discolored or if other foreign particulate matter is present.
3. Withdraw the proper volume of CINQAIR from the vial(s), based on the recommended weight-based dosage. Discard any unused portion.
4. Dispense syringe contents slowly into an infusion bag containing 50 mL of 0.9% Sodium Chloride Injection, USP to minimize foaming of CINQAIR (CINQAIR is compatible with polyvinylchloride (PVC) or polyolefin infusion bags). Gently invert the bag to mix the solution. Do not shake. Do not mix or dilute with other drugs.
5. Administer immediately after preparation. If not used immediately, store diluted solutions of CINQAIR in the refrigerator at 2°C to 8°C (36°F to 46°F) or at room temperature up to 25ºC (77ºF), protected from light, for up to 16 hours. The time between preparation of CINQAIR and administration should not exceed 16 hours.

Administration instructions

1. CINQAIR should be administered by a healthcare professional prepared to manage anaphylaxis [see Warnings and Precautions (5.1)].
2. If refrigerated prior to administration, allow the diluted CINQAIR solution to reach room temperature.
3. Use an infusion set with an in-line, low protein-binding filter (pore size of 0.2 micron). CINQAIR is compatible with polyethersulfone (PES), polyvinylidene fluoride (PVDF), nylon, and cellulose acetate in-line infusion filters.
4. Infuse the diluted solution of CINQAIR intravenously, over a 20 to 50 minute period. Infusion time may vary depending on the total volume to be infused as based upon patient weight.
5. Do not infuse CINQAIR concomitantly in the same intravenous line with other agents. No physical or biochemical compatibility studies have been conducted to evaluate the co-administration of CINQAIR with other agents.
6. Observe the patient over the infusion and for an appropriate period of time following infusion.
7. Upon completion of the infusion, flush the intravenous administration set with 0.9% Sodium Chloride Injection, USP to ensure that all CINQAIR has been administered.

3 DOSAGE FORMS AND STRENGTHS

Injection: 100 mg/10 mL (10 mg/mL), clear to slightly hazy/opalescent, colorless to slightly yellow solution in single-use vials.

4 CONTRAINDICATIONS

CINQAIR is contraindicated in patients who have known hypersensitivity to reslizumab or any of its excipients [see Warnings and Precautions (5.1)].

5 WARNINGS AND PRECAUTIONS

5.1 Anaphylaxis

Anaphylaxis to CINQAIR was reported in 0.3% of asthma patients in placebo-controlled clinical studies [see Adverse Reactions (6.1)]. These events were observed during or within 20 minutes after completion of the CINQAIR infusion and reported as early as the second dose of CINQAIR. Manifestations included dyspnea, decreased oxygen saturation, wheezing, vomiting, and skin and mucosal involvement, including urticaria. In all 3 cases, CINQAIR was discontinued.

Anaphylaxis can be life-threatening. CINQAIR should be administered by a healthcare professional prepared to manage anaphylaxis. Patients should be observed for an appropriate period of time after CINQAIR administration. If severe systemic reactions, including anaphylaxis, occur, stop administration of CINQAIR immediately and provide appropriate medical treatment. Prior to CINQAIR administration, inform patients of the signs and symptoms of anaphylaxis and instruct them to seek immediate medical care if symptoms occur. Discontinue CINQAIR use permanently if the patient experiences signs or symptoms of anaphylaxis [see Contraindications (4)].

5.2 Acute Asthma Symptoms or Deteriorating Disease

CINQAIR should not be used to treat acute asthma symptoms or acute exacerbations. Do not use CINQAIR to treat acute bronchospasm or status asthmaticus. Patients should seek medical advice if their asthma remains uncontrolled or worsens after initiation of treatment with CINQAIR.

5.3 Malignancy

In placebo-controlled clinical studies, 6/1028 (0.6%) patients receiving 3 mg/kg CINQAIR had at least 1 malignant neoplasm reported compared to 2/730 (0.3%) patients in the placebo group. The observed malignancies in CINQAIR-treated patients were diverse in nature and without clustering of any particular tissue type. The majority of malignancies were diagnosed within less than six months of exposure to CINQAIR.

5.4 Reduction of Corticosteroid Dosage

No clinical studies have been conducted to assess reduction of maintenance corticosteroid dosages following administration of CINQAIR. Do not discontinue systemic or inhaled corticosteroids abruptly upon initiation of therapy with CINQAIR. Reductions in corticosteroid dose, if appropriate, should be gradual and performed under the supervision of a physician. Reduction in corticosteroid dose may be associated with systemic withdrawal symptoms and/or unmask conditions previously suppressed by systemic corticosteroid therapy.

5.5 Parasitic (Helminth) Infection

Eosinophils may be involved in the immunological response to some helminth infections. Patients with known parasitic infections were excluded from participation in clinical studies. It is unknown if CINQAIR will influence the immune response against parasitic infections. Treat patients with pre-existing helminth infections before initiating CINQAIR. If patients become infected while receiving treatment with CINQAIR and do not respond to anti-helminth treatment, discontinue treatment with CINQAIR until infection resolves.

6 ADVERSE REACTIONS

The following adverse reactions are discussed in other sections of the labeling:

- Anaphylaxis [see Warnings and Precautions (5.1)]
- Malignancy [see Warnings and Precautions (5.3)]

6.1 Clinical Trials Experience

Because clinical trials are conducted under widely varying conditions, adverse reaction rates observed in the clinical trials of a drug cannot be directly compared to rates in the clinical trials of another drug and may not reflect the rates observed in clinical practice.

Overall, 2195 subjects received at least 1 dose of CINQAIR. The data described below reflect exposure to CINQAIR in 1611 patients with asthma, including 1120 exposed for up to 16 weeks, 1006 exposed for 6 months, 759 exposed for 1 year, and 249 exposed for longer than 2 years. The above referenced safety exposure for CINQAIR is derived from placebo-controlled studies ranging from 15 to 52 weeks in duration (CINQAIR 0.3 mg/kg and 3 mg/kg [n=1131] and placebo [n=730]) and 480 new CINQAIR 3 mg/kg exposures (previously on placebo) from a single open-label extension study (n=1051). While a lower dose of CINQAIR 0.3 mg/kg (n=103) was included in a clinical trial, 3 mg/kg is the only recommended dose [see Dosage and Administration (2.1)]. Of the 1611 patients, 1596 received the 3 mg/kg dose, 1028 of which were in the placebo-controlled studies. In the placebo-controlled asthma studies, the population studied was 12 to 76 years of age, 62% female, and 73% white. While subjects aged 12 to 17 years were included in these trials, CINQAIR is not approved for use in this age group [see Use in Specific Populations (8.4)].

Serious adverse reactions that occurred in placebo-controlled studies in more than 1 subject and in a greater percentage of subjects treated with CINQAIR (n=1131) than placebo (n=730) included anaphylaxis (3 subjects vs. 0 subjects, respectively). The 3 subjects who experienced anaphylaxis were discontinued from the clinical studies [see Warnings and Precautions (5.1)]. Malignancy also occurred more commonly in patients treated with CINQAIR than placebo (0.6% and 0.3%, respectively) [see Warnings and Precautions (5.3)].

Adverse reactions that occurred at greater than or equal to 2% incidence and more commonly than in the placebo group included 1 event: oropharyngeal pain (2.6% vs. 2.2%).

CPK elevations and muscle-related adverse reactions

Elevated baseline creatine phosphokinase (CPK) was more frequent in patients randomized to CINQAIR (14%) versus placebo (9%). Transient CPK elevations in patients with normal baseline CPK values were observed more frequently with CINQAIR (20%) versus placebo (18%) during routine laboratory assessments. CPK elevations >10 x ULN, regardless of baseline CPK value, were 0.8% in the CINQAIR group compared to 0.4% in the placebo group. CPK elevations >10 x ULN were asymptomatic and did not lead to treatment discontinuation.

Myalgia was reported in 1% (10/1028) of patients in the CINQAIR 3 mg/kg group compared to 0.5% (4/730) of patients in the placebo group. On the day of infusion, musculoskeletal adverse reactions were reported in 2.2% and 1.5% of patients treated with CINQAIR 3 mg/kg and placebo, respectively. These reactions included (but were not limited to) musculoskeletal chest pain, neck pain, muscle spasms, extremity pain, muscle fatigue, and musculoskeletal pain.

6.2 Immunogenicity

As with all therapeutic proteins, there is a potential for immunogenicity. In placebo-controlled studies, a treatment-emergent anti-reslizumab antibody response developed in 53/983 (5.4%) of CINQAIR-treated patients (3 mg/kg). In the long-term, open-label study, treatment-emergent anti-reslizumab antibodies were detected in 49/1014 (4.8%) of CINQAIR-treated (3 mg/kg) asthma patients over 36 months. The antibody responses were of low titer and often transient. Neutralizing antibodies were not evaluated. There was no detectable impact of the antibodies on the clinical pharmacokinetics, pharmacodynamics, clinical efficacy, and safety of CINQAIR [see Clinical Pharmacology (12.2)]. Product-specific IgE antibodies were not detected in patients who reported anaphylactic reactions.

The data reflect the percentage of patients whose test results were positive for antibodies to reslizumab in specific assays. The observed incidence of antibody response is highly dependent on several factors, including assay sensitivity and specificity, assay methodology, sample handling, timing of sample collection, concomitant medication, and underlying disease. For these reasons, comparison of the incidence of antibodies to reslizumab with the incidence of antibodies to other products may be misleading.

7 DRUG INTERACTIONS

No formal clinical drug interaction studies have been performed with CINQAIR.

8 USE IN SPECIFIC POPULATIONS

8.1 Pregnancy

Risk Summary

The data on pregnancy exposure from the clinical trials are insufficient to inform on drug-associated risk. Monoclonal antibodies, such as reslizumab, are transported across the placenta in a linear fashion as pregnancy progresses; therefore, potential effects on a fetus are likely to be greater during the second and third trimester of pregnancy. Reslizumab has a long half-life [see Clinical Pharmacology (12.3)]. This should be taken into consideration.

In animal reproduction studies, there was no evidence of embryo-fetal adverse developmental effects with intravenous administration of reslizumab during organogenesis to pregnant mice and rabbits at doses that produced exposures up to approximately 6 times the exposure at the maximum recommended human dose (MRHD) in mice and approximately 17 times the exposure at the MRHD in rabbits [see Data].

The estimated background risk of major birth defects and miscarriage for the indicated population(s) are unknown. In the U.S. general population, the estimated background risk of major birth defects and miscarriage in clinically recognized pregnancies is 2 to 4% and 15 to 20%, respectively.

Clinical Considerations

Disease-Associated Maternal and/or Embryo-Fetal Risk

In women with poorly or moderately controlled asthma, evidence demonstrates that there is an increased risk of preeclampsia in the mother and prematurity, low birth weight, and small for gestational age in the neonate. The level of asthma control should be closely monitored in pregnant women and treatment adjusted as necessary to maintain optimal control.

Data

Animal Data

In 2 separate embryo-fetal development studies, pregnant mice and rabbits received a single reslizumab dose during the period of organogenesis at 2, 10, and 50 mg/kg (0.4, 1.5, and 6 times the exposures achieved at the MRHD in mice on an AUC basis and 0.67, 3.3, and 17 times the exposures achieved at the MRHD in rabbits on a mg/kg basis). Reslizumab was not teratogenic in mice or rabbits. Embryo-fetal development of interleukin-5 (IL-5) deficient mice has been reported to be generally unaffected relative to wild-type mice.

In a prenatal and postnatal development study, pregnant CD-1 mice received reslizumab during organogenesis on gestation days 6 and 18 and on postnatal day 14 at 10 or 50 mg/kg (1.5 and 6 times the exposures achieved at the MRHD on an AUC basis). Reslizumab did not have any effects on fetal development up to approximately 4 months after birth. Reslizumab crossed the placenta of pregnant mice. Serum concentrations in pups were approximately 6 to 8% of those in the dams (parental female mice) on postnatal day 14.

8.2 Lactation

Risk Summary

It is not known whether reslizumab is present in human milk, and the effects of reslizumab on the breast fed infant and on milk production are not known. However, human IgG is known to be present in human milk. Reslizumab was present in the milk of lactating mice following dosing during pregnancy [see Data]. The developmental and health benefits of breastfeeding should be considered along with the mother’s clinical need for CINQAIR and any potential adverse effects on the breast-fed child from CINQAIR or the underlying maternal condition.

Data

Reslizumab was excreted in milk of lactating CD-1 mice that received reslizumab at 10 or 50 mg/kg (1.5 and 6 times the exposures achieved at the MRHD on an AUC basis) during pregnancy on gestation days 6 and 18 and on postnatal day 14. Levels of reslizumab in milk were approximately 5-7% of maternal serum concentrations.

8.4 Pediatric Use

CINQAIR is not indicated for use in pediatric patients less than 18 years of age. The safety and effectiveness in pediatric patients (aged 17 years and younger) have not been established.

CINQAIR was evaluated in 39 patients aged 12 to less than 18 years with asthma in two 52-week exacerbation studies and one 16-week lung function study. In the exacerbation studies, patients were required to have at least 1 asthma exacerbation requiring systemic corticosteroid use in the year prior to study entry. In these studies, the asthma exacerbation rate was higher in adolescent patients treated with CINQAIR than placebo (CINQAIR n=14, rate 2.86, 95% CI [1.02 to 8.09] and placebo n=11, rate 1.37, 95% CI [0.57 to 3.28]: rate ratio 2.09, 95% CI [0.82 to 5.36]).

8.5 Geriatric Use

CINQAIR was evaluated in 122 patients aged 65 years and older with asthma in two 52-week exacerbation studies and two 16-week lung function studies. No overall differences in safety or effectiveness were observed between these patients and younger patients. Based on available data, no adjustment of the dosage of CINQAIR in geriatric patients is necessary.

10 OVERDOSAGE

Single doses of up to 732 mg have been administered intravenously to subjects in clinical trials without evidence of dose-related toxicities.

There is no specific treatment for an overdose with CINQAIR. If overdose occurs, the patient should be treated supportively with appropriate monitoring as necessary.

11 DESCRIPTION

CINQAIR (reslizumab) is a humanized interleukin-5 antagonist monoclonal antibody (IgG4κ). Reslizumab is produced by recombinant DNA technology in murine myeloma non-secreting 0 (NS0) cells. Reslizumab has a molecular weight of approximately 147 kDa.

CINQAIR is a sterile, preservative-free, clear to slightly hazy/opalescent, colorless to slightly yellow solution (injection) for intravenous infusion. Since CINQAIR is a protein, proteinaceous particles may be present in the solution that appear as translucent to white, amorphous particulates. Each single-use vial contains 100 mg reslizumab in 10 mL. Each mL contains 10 mg of reslizumab, glacial acetic acid (0.12 mg), sodium acetate trihydrate (2.45 mg), and sucrose (70 mg), with a pH of 5.5.

12 CLINICAL PHARMACOLOGY

12.1 Mechanism of Action

Reslizumab is an interleukin-5 antagonist (IgG4, kappa). IL-5 is the major cytokine responsible for the growth and differentiation, recruitment, activation, and survival of eosinophils. Reslizumab binds to IL-5 with a dissociation constant of 81 pM, inhibiting the bioactivity of IL-5 by blocking its binding to the alpha chain of the IL-5 receptor complex expressed on the eosinophil surface. Inflammation is an important component in the pathogenesis of asthma. Multiple cell types (e.g., mast cells, eosinophils, neutrophils, macrophages, lymphocytes) and mediators (e.g., histamine, eicosanoids, leukotrienes, cytokines) are involved in inflammation. Reslizumab, by inhibiting IL-5 signaling, reduces the production and survival of eosinophils; however, the mechanism of reslizumab action in asthma has not been definitively established.

12.2 Pharmacodynamics

In clinical studies with CINQAIR 3 mg/kg, reductions in blood eosinophil counts were observed following the first dose and maintained through 52 weeks of treatment with no signs of tachyphylaxis. Mean eosinophil counts were 696 cells/mcL (n=245) and 624 cells/mcL (n=244) at baseline, and were 55 cells/mcL (92% reduction, n=212) and 496 cells /mcL (21% reduction, n=212) at the Week 52 visit for the CINQAIR and placebo treatment groups, respectively. Early eosinophil reduction was apparent in a subset of patients who had blood eosinophil counts assessed at days 2-3: 220 cells/mcL and 610/mcL for CINQAIR (n=35) and placebo (n=32), respectively. Eosinophils returned towards baseline in those CINQAIR-treated patients who completed a 90-day follow-up assessment (n=35, 480 cells/mcL), approximately 120 days after the last dose of CINQAIR.

Reductions of blood eosinophils were related to reslizumab serum levels, i.e., greater reductions of blood eosinophils were observed in subjects with higher reslizumab serum concentrations.

Treatment-emergent anti-reslizumab antibodies did not interfere with the blood eosinophil reduction effect by reslizumab.

12.3 Pharmacokinetics

The pharmacokinetics (PK) of reslizumab were characterized in healthy adults (n=130), in patients with asthma (n=438), and in other patient populations (n=236). The PK characteristics of reslizumab were similar across these populations. Inter-individual variability in peak and overall exposure was approximately 20-30%.

Peak serum concentrations were typically observed at the end of the infusion. Serum reslizumab concentrations generally declined from peak in a biphasic manner. Following multiple doses, serum concentrations of reslizumab accumulated approximately 1.5 to 1.9-fold.

Systemic exposure to reslizumab appeared to be unaffected by the presence of treatment-emergent anti-reslizumab antibodies.

Distribution

Reslizumab has a volume of distribution of approximately 5 liters, suggesting minimal distribution to the extravascular tissues.

Metabolism

Similar to other monoclonal antibodies, reslizumab is degraded by enzymatic proteolysis into small peptides and amino acids. As reslizumab binds to a soluble target, it is not expected to go through a target-mediated clearance.

Elimination

Reslizumab clearance was approximately 7 mL/hour. Reslizumab has a half-life of about 24 days.

Specific Populations

Age, Race, and Gender

Population PK analyses demonstrated that there was no significant effect of age, race, or gender on the PK of reslizumab.

Hepatic Impairment

No clinical studies were conducted to assess the effect of hepatic impairment on the PK of reslizumab. The results of population PK analyses indicated that there was no significant difference in the PK of reslizumab between patients with normal liver function tests (total bilirubin less than or equal to the ULN and aspartate aminotransferase [AST] less than or equal to the ULN) and mildly increased liver function tests (total bilirubin above the ULN and less than or equal to 1.5-times the ULN or AST greater than ULN and total bilirubin less than or equal to the ULN).

Renal Impairment

No clinical studies have been conducted to assess the effect of renal impairment on the PK of reslizumab. The results of population PK analyses indicated that there was no significant difference in the PK of reslizumab between patients with normal renal function (estimated glomerular filtration rate [eGFR] greater than or equal to 90 mL/min/1.73 m^2), mild renal impairment (eGFR 60-89 mL/min/1.73 m^2), and moderate renal impairment (eGFR 30-59 mL/min/1.73 m^2).

Drug Interactions

In vitro data indicate that IL-5 and reslizumab are unlikely to affect CYP1A2, 2B6, or 3A4 enzyme activity.

No formal clinical drug interaction studies have been conducted with reslizumab. Population PK analyses indicate that concomitant use of either leukotriene antagonists or corticosteroids does not affect the PK of reslizumab.

13 NONCLINICAL TOXICOLOGY

13.1 Carcinogenesis, Mutagenesis, Impairment of Fertility

In a 6-month bioassay, reslizumab was administered intravenously once every 2 weeks for 26 consecutive weeks (14 total doses) to Tg.rasH2 mice at doses up to 516 mg/kg/dose. There was no evidence of carcinogenicity.

Published literature using animal models suggests that IL-5 and eosinophils are part of an early inflammatory reaction at the site of tumorigenesis and can promote tumor rejection. However, other reports indicate that eosinophil infiltration into tumors can promote tumor growth. Therefore, the malignancy risk in humans from an antibody to IL-5 such as reslizumab is unknown.

In a fertility study, administration of reslizumab to parental mice at doses up to 50 mg/kg (approximately 6 times the MRHD on an AUC basis) had no effects on male or female mating or fertility.

14 CLINICAL STUDIES

The asthma development program for CINQAIR 3 mg/kg (administered once every 4 weeks) included 4 randomized, double-blind, placebo-controlled studies (Studies I-IV) 16 to 52 weeks in duration involving 981 patients 12 years of age and older. While patients aged 12 to 17 years were included in these trials, CINQAIR is not approved for use in this age group [see Use in Specific Populations (8.4)]. All subjects continued their background asthma therapy throughout the duration of the studies.

Studies I and II

Studies I and II were 52-week studies in 953 patients with asthma who were required to have a blood eosinophil count of at least 400/mcL (within 3 to 4 weeks of dosing), and at least 1 asthma exacerbation requiring systemic corticosteroid use over the past 12 months. The majority of patients (82%) were on medium-high dose inhaled corticosteroids plus a long-acting beta agonist (ICS/LABA) at baseline. Maintenance oral corticosteroids (OCS) (up to 10 mg of prednisone per day or equivalent) were allowed; 106 (11%) patients were on OCS at baseline. CINQAIR 3 mg/kg administered once every 4 weeks for a total of 13 doses was evaluated compared with placebo.

Study III

Study III was a 16-week study in 315 patients who were required to have a blood eosinophil count of at least 400/mcL at screening (within 3 to 4 weeks of dosing). Maintenance OCS were not allowed. CINQAIR 3 mg/kg or 0.3 mg/kg administered once every 4 weeks for a total of 4 doses was evaluated compared with placebo. While 2 doses of CINQAIR were studied, CINQAIR 3 mg/kg is the only recommended dose [see Dosage and Administration (2.1)].

Study IV

Study IV was a 16-week study in 496 patients unselected for baseline blood eosinophil levels (approximately 80% of patients had a screening [within 3 to 4 weeks of dosing] blood eosinophil count of less than 400/mcL). Maintenance OCS were not allowed. CINQAIR 3 mg/kg administered once every 4 weeks for a total of 4 doses was evaluated compared with placebo.

The demographics and baseline characteristics of these 4 studies is provided in Table 1.

Table 1: Demographics and Baseline Characteristics of Patients in Asthma Studies

 | Study I (N=489) | Study II (N=464) | Study III (N=315) | Study IV (N=496)
Mean age (yr) | 47 | 47 | 44 | 45
Female (%) | 63 | 63 | 58 | 64
White (%) | 73 | 73 | 81 | 67
Duration of asthma, mean (yr) | 19 | 18 | 20 | 26
Baseline Pre-bronchodilator FEV1, mean % predicted [Baseline for lung function and eosinophil count is the day of randomization.] | 64 | 69 | 70 | 67
Baseline Reversibility, mean % ΔFEV1 post-SABA | 26 | 28 | 25 | 26
Baseline mean blood eosinophil count/mcL | 660 | 649 | 614 | 280
Mean number of exacerbations in previous year | 1.99 | 1.94 | 2.03 | 1.86

FEV1=forced expiratory volume in 1 second; SABA=short-acting beta agonist.

All patients had to be on inhaled corticosteroid (ICS) background therapy and could have been receiving any combination of background therapies (ICS with or without another controller [non-ICS and/or OCS]).

Exacerbations

The primary endpoint for Studies I and II was the frequency of asthma exacerbations for each patient during the 52-week treatment period. An asthma exacerbation was defined as a worsening of asthma that required at least 1 of the following medical interventions:

1) Either the use of a systemic corticosteroid, or ≥ 2-fold an increase in the use of ICS for 3 or more days, and/or

2) Asthma-related emergency treatment including at least 1 of the following: an unscheduled visit to their healthcare professional for nebulizer treatment or other urgent treatment to prevent worsening of asthma symptoms; a visit to the emergency room for asthma-related treatment; or an asthma-related hospitalization.

The medical intervention had to be corroborated with at least 1 of the following: 1) a decrease in forced expiratory volume in 1 second (FEV1) by 20% or more from baseline, 2) a decrease in peak expiratory flow rate (PEFR) by 30% or more from baseline on 2 consecutive days, or 3) worsening of symptoms or other clinical signs per physician evaluation of the event.

In Studies I and II, patients receiving CINQAIR 3 mg/kg administered once every 4 weeks had significant reductions in the rate of all asthma exacerbations compared to placebo (Table 2). Exacerbations requiring the use of a systemic corticosteroid (e.g., OCS) as well as exacerbations resulting in hospitalization or an emergency room visit were each reduced with CINQAIR 3 mg/kg.

Table 2: Frequency of Asthma Exacerbations during the 52-Week Treatment Period in Patients with Severe Asthma with an Eosinophilic Phenotype (Studies I and II) [Randomized patients]
 | Treatment Arm | Asthma Exacerbation Rate | Rate Ratio (95% CI)
All exacerbations
Study I | CINQAIR 3 mg/kg (n=245) | 0.90 | 0.5; (0.37, 0.67)
Study I | Placebo (n=244) | 1.80 | 0.5; (0.37, 0.67)
Study II | CINQAIR 3 mg/kg (n=232) | 0.86 | 0.41; (0.28, 0.59)
Study II | Placebo (n=232) | 2.11 | 0.41; (0.28, 0.59)
Exacerbations requiring systemic corticosteroid use
Study I | CINQAIR 3 mg/kg (n=245) | 0.72 | 0.45; (0.33, 0.62)
Study I | Placebo (n=244) | 1.60 | 0.45; (0.33, 0.62)
Study II | CINQAIR 3 mg/kg (n=232) | 0.65 | 0.39; (0.27, 0.58)
Study II | Placebo(n=232) | 1.66 | 0.39; (0.27, 0.58)
Exacerbations resulting in a hospitalization and/or emergency room visit
Study I | CINQAIR 3 mg/kg (n=245) | 0.14 | 0.66; (0.32, 1.36)
Study I | Placebo(n=244) | 0.21 | 0.66; (0.32, 1.36)
Study II | CINQAIR 3 mg/kg (n=232) | 0.03 | 0.69; (0.29, 1.65)
Study II | Placebo (n=232) | 0.05 | 0.69; (0.29, 1.65)

The proportion of patients who did not experience an asthma exacerbation during the 52-week treatment period was higher in the CINQAIR 3 mg/kg group (62% and 75%) compared with the placebo group (46% and 55%), in Studies I and II, respectively. The time to first asthma exacerbation was significantly longer for the groups receiving CINQAIR 3 mg/kg compared with placebo in both Studies I and II. A representative figure from Study I is shown below (Figure 1). Study II showed similar results.

Figure 1: Time to First Asthma Exacerbation by Treatment Group in Patients with Severe Asthma with an Eosinophilic Phenotype (Study I)

Lung Function

The effect of CINQAIR 3 mg/kg administered once every 4 weeks on FEV1 over time relative to placebo was assessed in all 4 studies (Table 3). FEV1 was the primary endpoint in the 16-week lung function studies: Study III (Figure 2) and Study IV.

Study III also studied a lower dose, CINQAIR 0.3 mg/kg, that produced significant but numerically smaller changes in FEV1 and blood eosinophil reduction compared with the 3 mg/kg dose. While 2 doses of CINQAIR were studied, CINQAIR 3 mg/kg is the only recommended dose [see Dosage and Administration (2.1)].

Study IV was the only study to test CINQAIR 3 mg/kg in asthma patients unselected for blood eosinophils (measured 3 to 4 weeks prior to dosing); association of treatment effect (i.e., difference between CINQAIR and placebo in the change in FEV1 at Week 16) and baseline blood eosinophils was not observed.

Table 3: Mean Change (95% CI) from Baseline in FEV1 in mL Over 16 Weeks (Difference from CINQAIR and Placebo) in Patients with Severe Asthma with an Eosinophilic Phenotype

Study | FEV1 Change in mL
Study I | 137 (76, 198)
Study II | 93 (30, 155)
Study III | 160 (60, 259)
Study IV [Study IV studied asthma patients unselected for blood eosinophils] | 76 (-6,158)

Improvements in FEV1 were observed at 4 weeks following the first dose of CINQAIR for Studies I and II and maintained through Week 52.

Figure 2: Mean Change from Baseline in FEV1 in Patients with Severe Asthma with an Eosinophilic Phenotype (Study III)

The Asthma Control Questionnaire-7 (ACQ-7) and Asthma Quality of Life Questionnaire (AQLQ) were both assessed in Studies I, II, and III. The responder rate for both measures was defined as an improvement in score of 0.5 or more as threshold over 16 weeks.

- For ACQ-7, the responder rate for those randomized to CINQAIR vs. placebo was 69% vs. 65% for Study I, 70% vs. 58% for Study II, and 64% vs. 58% for Study III.
- For AQLQ, the responder rate for those randomized to CINQAIR vs. placebo was 66% vs. 58% for Study I, 67% vs. 55% for Study II, and 64% vs. 48% for Study III.

16 HOW SUPPLIED/STORAGE AND HANDLING

CINQAIR (reslizumab) injection, 100 mg/10 mL (10 mg/mL), is supplied as a preservative-free, sterile, clear to slightly hazy/opalescent, colorless to slightly yellow solution in single-use vials. The following packaging configuration is available:

- NDC 59310-610-31: 100 mg/10 mL (10 mg/mL) single-use vial.

Storage and Stability: Refrigerate at 2 ºC to 8ºC (36°F to 46°F). Do not freeze. Do not shake. Protect the vials from light by storing in the original package until time of use.

17 PATIENT COUNSELING INFORMATION

See FDA approved patient labeling (Patient Information).

Hypersensitivity/Anaphylaxis

Inform patients that hypersensitivity reactions, including anaphylaxis, have occurred with administration of CINQAIR. Educate patients on the signs and symptoms of hypersensitivity reactions and anaphylaxis (e.g., skin or mucosal involvement, airway compromise, reduced blood pressure). Instruct patients to contact their healthcare professional immediately if they experience symptoms of an allergic reaction after they have received their infusion of CINQAIR [see Warnings and Precautions (5.1)].

Not for Acute Symptoms or Deteriorating Disease

Inform patients that CINQAIR does not treat acute asthma symptoms or acute exacerbations. Inform patients to seek medical advice if their asthma remains uncontrolled or worsens after initiation of treatment with CINQAIR [see Warnings and Precautions (5.2)].

Malignancy

Counsel CINQAIR-treated patients about the risk of malignancies [see Warnings and Precautions (5.3)].

Reduction of Corticosteroid Dosage

Inform patients not to discontinue systemic or inhaled corticosteroids except under the direct supervision of a physician. Inform patients that reduction in corticosteroid dose may be associated with systemic withdrawal symptoms and/or unmask conditions previously suppressed by systemic corticosteroid therapy [see Warnings and Precautions (5.4)].

Manufactured by:

Teva Respiratory, LLC

West Chester, PA 19380

U.S. License Number 2047

US Patent RE39,548 and 6,056,957

©2020 Teva Respiratory, LLC

CNQ-004

Patient Package Insert

PATIENT INFORMATION

PATIENT INFORMATION

CINQAIR (sink-ayr’)

(reslizumab) injection for intravenous use

What is the most important information I should know about CINQAIR?

CINQAIR can cause serious side effects, including:

Serious allergic reactions (anaphylaxis). Serious allergic reactions can happen right after you receive your CINQAIR infusion. These reactions can cause death. Allergic reactions sometimes do not happen right away. Your healthcare provider will watch you during and after you receive your CINQAIR infusion for any signs of a reaction. Tell your healthcare provider right away if you have any of the following symptoms that may be associated with an allergic reaction:

• breathing problems • flushing • itching • symptoms of low blood pressure (fainting, dizziness, light headedness, confusion, fast heart beat)

• paleness • skin rash (hives) • swelling of your face, lips, mouth, or tongue • nausea or abdominal discomfort

What is CINQAIR?

CINQAIR is a prescription medicine used with other asthma medicines for the maintenance treatment of asthma in people aged 18 years of age and older whose asthma is not controlled with the current asthma medicines. When added to other medicines for asthma, CINQAIR helps prevent severe asthma attacks (exacerbations) and can improve your breathing. Medicines such as CINQAIR reduce blood eosinophils. Eosinophils are a type of white blood cell that may contribute to your asthma.

- CINQAIR is not used to treat other problems caused by eosinophils.
- CINQAIR is not used to treat sudden breathing problems.

It is not known if CINQAIR is safe and effective in children less than 18 years of age.

Do not receive CINQAIR if you are allergic to reslizumab or any of the ingredients in CINQAIR. See the end of this leaflet for a complete list of ingredients in CINQAIR.

Before receiving CINQAIR, tell your healthcare provider about all of your medical conditions, including if you:

- are taking oral or inhaled corticosteroid medicines. Do not stop taking your corticosteroid unless your healthcare provider tells you to stop. This may cause other symptoms that were controlled by the corticosteroid medicine to come back.
- have or have had cancer (malignancy).
- have a parasitic (helminth) infection.
- are pregnant or plan to become pregnant. It is not known if CINQAIR will harm your unborn baby. Tell your healthcare provider if you become pregnant during your treatment with CINQAIR.
- are breastfeeding or plan to breastfeed. It is not known if CINQAIR passes into your breast milk. You and your healthcare provider should decide if you will receive CINQAIR and breastfeed. Talk to your healthcare provider about the best way to feed your baby if you receive CINQAIR.

Tell your healthcare provider about all the medicines you take, including prescription and over-the-counter medicines, vitamins, and herbal supplements.

Do not stop taking your other asthma medicines unless your healthcare provider tells you to.

How will I receive CINQAIR?

- You will be given CINQAIR by a healthcare provider using a needle placed in a vein (intravenous infusion) 1 time every 4 weeks. It will take about 20 to 50 minutes to receive the full dose of CINQAIR.

What are the possible side effects of CINQAIR?

CINQAIR may cause serious side effects, including:

- See “What is the most important information I should know about CINQAIR?”
- abnormal growth of cells or tissue in your body that may or may not be cancer (malignancy)

The most common side effects of CINQAIR include throat pain.

These are not all the possible side effects of CINQAIR.

Call your doctor for medical advice about side effects. You may report side effects to FDA at 1-800-FDA-1088.

General information about the safe and effective use of CINQAIR.

Medicines are sometimes prescribed for purposes other than those listed in a Patient Information leaflet. Do not use CINQAIR for a condition for which it was not prescribed. You can ask your pharmacist or healthcare provider for information about CINQAIR that is written for healthcare professionals.

What are the ingredients in CINQAIR?

Active ingredient: reslizumab

Inactive ingredients: sodium acetate, acetic acid, sucrose

Manufactured by: Teva Respiratory, LLC; West Chester, PA 19380

U.S. License Number 2047

©2020 Teva Respiratory, LLC

CNQPL-003

For more information, go to www.CINQAIR.com or call 1-888-483-8279.

This Patient Information has been approved by the U.S. Food and Drug Administration

Revised: 02/2020

Package/Label Display Panel NDC 59310-610-31

NDC 59310-610-31

Rx only

Must be Refrigerated Sterile

CINQAIR® (reslizumab) Injection 100 mg/10 mL (10 mg/mL)

For Intravenous Infusion Only

Dilute Prior to Administration

One Single-Use Vial

Discard Unused Portion

TEVA

Package/Label Display Panel NDC 59310-610-33

NDC 59310-610-33

Rx only

Must be Refrigerated

Sterile

CINQAIR® (reslizumab) Injection 100 mg/10 mL (10 mg/mL)

For Intravenous Infusion Only

Dilute Prior to Administration

One Single-Use Vial

Discard Unused Portion

TEVA